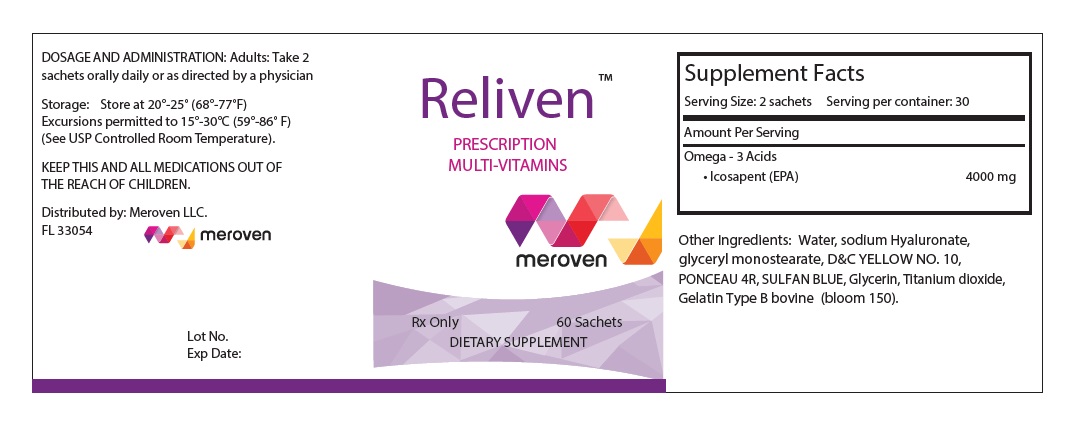 DRUG LABEL: RELIVEN
NDC: 74653-001 | Form: CAPSULE, COATED PELLETS
Manufacturer: Meroven Llc
Category: other | Type: DIETARY SUPPLEMENT
Date: 20210302

ACTIVE INGREDIENTS: ICOSAPENT 4000 mg/2 1
INACTIVE INGREDIENTS: WATER; HYALURONATE SODIUM; GLYCERYL MONOSTEARATE; D&C YELLOW NO. 10; PONCEAU 4R; SULFAN BLUE; GLYCERIN; TITANIUM DIOXIDE; GELATIN TYPE B BOVINE (150 BLOOM)

Reliven™ PRESCRIPTION MULTI-VITAMINS DIETARY SUPPLEMENT

HEALTH CLAIM: Reliven PRESCRIPTION MULTI-VITAMINS DIETARY SUPPLEMENT meroven Rx Only Distributed by: Meroven LLC. FL 33054

Supplement Facts

Serving Size: 2 sachets Serving per container: 30

Amount Per Serving

Omega - 3 Acids

• Icosapent (EPA) 4000 mg

Other Ingredients: Water, sodium Hyaluronate, glycerly monostearate, D&C YELLOW NO. 10, PONCEAU 4R, SULFAN BLUE, Glycerin, Titanium dioxide, Gelatin Type B bovine (bloom 150).

WARNINGS

KEEP THIS AND ALL MEDICATIONS OUT OF THE REACH OF CHILDREN.

DOSAGE AND ADMINISTRATION:

Adults: Take 2 sachets orally daily or as directed by a physician

Storage:

Store at 20°-25° (68°-77°F)

Excursions permitted to 15°-30°C (59°-86°F)

(See USP Controlled Room Temperature).